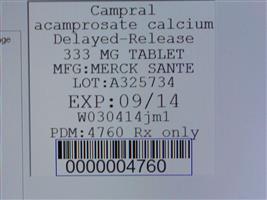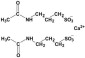 DRUG LABEL: Campral
NDC: 68151-4760 | Form: TABLET, DELAYED RELEASE
Manufacturer: Carilion Materials Management
Category: prescription | Type: HUMAN PRESCRIPTION DRUG LABEL
Date: 20160806

ACTIVE INGREDIENTS: acamprosate calcium 333 mg/1 1
INACTIVE INGREDIENTS: CROSPOVIDONE; CELLULOSE, MICROCRYSTALLINE; MAGNESIUM SILICATE; SODIUM STARCH GLYCOLATE TYPE A POTATO; SILICON DIOXIDE; MAGNESIUM STEARATE; TALC; PROPYLENE GLYCOL; METHACRYLIC ACID - ETHYL ACRYLATE COPOLYMER (1:1) TYPE A

HIGHLIGHTS OF PRESCRIBING INFORMATION

These highlights do not include all the information needed to use CAMPRAL safely and effectively. See full prescribing information for CAMPRAL. CAMPRAL® (acamprosate calcium) Delayed-Release Tablets Initial U.S. Approval: 2004

1 INDICATIONS AND USAGE

- Campral® is indicated for the maintenance of abstinence from alcohol in patients with alcohol dependence who are abstinent at treatment initiation (,). 114
- Treatment with Campral should be part of a comprehensive management program that includes psychosocial support (). 1

2 DOSAGE AND ADMINISTRATION

- Recommended dose: 666 mg (two 333 mg tablets) taken three times daily (). 2
- Dose reduction to one 333 mg tablet taken three times daily for patients with moderate renal impairment (creatinine clearance 30-50 mL/min) (). 2.1
- Campral is contraindicated in patients with severe renal impairment (creatinine clearance of ≤30 mL/min) (, , , ,). 2.14.25.18.612.3

3 DOSAGE FORMS AND STRENGTHS

Enteric-coated tablets, 333 mg (). 3

4 CONTRAINDICATIONS

- Campral is contraindicated in patients who previously have exhibited hypersensitivity to acamprosate calcium or any of its components (). 4.1
- Campral is contraindicated in patients with severe renal impairment (). 4.2

5 WARNINGS AND PRECAUTIONS

- Dose reduction is required for patients with moderate renal impairment (). 5.1
- Monitor patients for depression or suicidal ideation and prompt patients, families, and caregivers to report such symptoms to the health care provider (). 5.2

6 ADVERSE REACTIONS

Common adverse events that occurred in any Campral treatment group at a rate of 3% or greater and greater than the placebo group in controlled clinical trials with spontaneously reported adverse events are: accidental injury, asthenia, pain, anorexia, diarrhea, flatulence, nausea, anxiety, depression, dizziness, dry mouth, insomnia, paresthesia, pruritus and sweating (). 6.1

. To report SUSPECTED ADVERSE REACTIONS, contact Forest Laboratories, Inc. at 1-800-678-1605, or FDA at 1-800-FDA-1088 orwww.fda.gov/medwatch

8 USE IN SPECIFIC POPULATIONS

- Pregnancy: Campral should be used during pregnancy only if the potential benefit justifies the potential risk to the fetus (). 8.1
- Nursing Mothers: Caution should be exercised when Campral is administered to a nursing woman (). 8.3
- Renal Impairment: Dose reduction required for moderate renal impairment; contraindicated in severe renal impairment (, , , ,) 2.14.25.18.612.3

FULL PRESCRIBING INFORMATION

1 INDICATIONS AND USAGE

Campral® is indicated for the maintenance of abstinence from alcohol in patients with alcohol dependence who are abstinent at treatment initiation. Treatment with Campral should be part of a comprehensive management program that includes psychosocial support.

The efficacy of Campral in promoting abstinence has not been demonstrated in subjects who have not undergone detoxification and not achieved alcohol abstinence prior to beginning Campral treatment. The efficacy of Campral in promoting abstinence from alcohol in polysubstance abusers has not been adequately assessed.

2 DOSAGE AND ADMINISTRATION

The recommended dose of Campral is two 333 mg tablets (each dose should total 666 mg) taken three times daily. A lower dose may be effective in some patients.

Although dosing may be done without regard to meals, dosing with meals was employed during clinical trials and is suggested in those patients who regularly eat three meals daily.

Treatment with Campral should be initiated as soon as possible after the period of alcohol withdrawal, when the patient has achieved abstinence, and should be maintained if the patient relapses. Campral should be used as part of a comprehensive psychosocial treatment program.

2.1 Dosage in Renal Impairment

For patients with moderate renal impairment (creatinine clearance of 30-50 mL/min), a starting dose of one 333 mg tablet taken three times daily is recommended. Campral is contraindicated in patients with severe renal impairment (creatinine clearance of ≤30 mL/min) [ and ]. see Contraindications (), Warnings and Precautions (), Use in Specific Populations (), 4.25.18.6 Clinical Pharmacology () 12.3

3 DOSAGE FORMS AND STRENGTHS

Campral 333 mg tablets are enteric-coated, white, round, biconvex tablets, identified with “333” debossed on one side.

4 CONTRAINDICATIONS

4.1 Hypersensitivity to Acamprosate Calcium

Campral is contraindicated in patients who previously have exhibited hypersensitivity to acamprosate calcium or any of its components.

4.2 Severe Renal Impairment

Campral is contraindicated in patients with severe renal impairment (creatinine clearance of ≤30 mL/min) [ and ]. see Dosage and Administration (), Warnings and Precautions (), Use in Specific Populations (), 2.15.18.6 Clinical Pharmacology () 12.3

5 WARNINGS AND PRECAUTIONS

5.1 Renal Impairment

Treatment with Campral in patients with moderate renal impairment (creatinine clearance of 30-50 mL/min) requires a dose reduction [ ]. Campral is contraindicated in patients with severe renal impairment (creatinine clearance of ≤30 mL/min) [ and ]. see Dosage and Administration () 2.1 see Dosage and Administration (), Contraindications (), Use in Specific Populations (), 2.14.28.6 Clinical Pharmacology () 12.3

5.2 Suicidality and Depression

In controlled clinical trials of Campral, adverse events of a suicidal nature (suicidal ideation, suicide attempts, completed suicides) were infrequent overall, but were more common in Campral-treated patients than in patients treated with placebo (1.4% vs. 0.5% in studies of 6 months or less; 2.4% vs. 0.8% in year-long studies). Completed suicides occurred in 3 of 2272 (0.13%) patients in the pooled acamprosate group from all controlled studies and 2 of 1962 patients (0.10%) in the placebo group. Adverse events coded as "depression" were reported at similar rates in Campral-treated and placebo-treated patients. Although many of these events occurred in the context of alcohol relapse, and the interrelationship between alcohol dependence, depression and suicidality is well-recognized and complex, no consistent pattern of relationship between the clinical course of recovery from alcoholism and the emergence of suicidality was identified. Alcohol-dependent patients, including those patients being treated with Campral, should be monitored for the development of symptoms of depression or suicidal thinking. Families and caregivers of patients being treated with Campral should be alerted to the need to monitor patients for the emergence of symptoms of depression or suicidality, and to report such symptoms to the patient's health care provider.

5.3 Alcohol Withdrawal

Use of Campral does not eliminate or diminish withdrawal symptoms.

6 ADVERSE REACTIONS

6.1 Clinical Trials Experience

Because clinical trials are conducted under widely varying conditions, adverse reaction rates observed in the clinical trials of a drug cannot be directly compared to rates in the clinical trials of another drug and may not reflect the rates observed in clinical practice.

Clinically significant serious adverse reactions associated with Campral described elsewhere in labeling include suicidality and depression and acute kidney failure [s , and ]. ee Warnings and Precautions () 5.2 Adverse Reactions () 6.2

The adverse event data described below reflect the safety experience in over 7000 patients exposed to Campral for up to one year, including over 2000 Campral-exposed patients who participated in placebo-controlled trials.

Adverse Events Leading to Discontinuation

In placebo-controlled trials of 6 months or less, 8% of Campral-treated patients discontinued treatment due to an adverse event, as compared to 6% of patients treated with placebo. In studies longer than 6 months, the discontinuation rate due to adverse events was 7% in both the placebo-treated and the Campral-treated patients. Only diarrhea was associated with the discontinuation of more than 1% of patients (2% of Campral-treated vs. 0.7% of placebo-treated patients). Other events, including nausea, depression, and anxiety, while accounting for discontinuation in less than 1% of patients, were nevertheless more commonly cited in association with discontinuation in Campral-treated patients than in placebo-treated patients.

Common Adverse Events Reported in Controlled Trials

Common adverse events were collected spontaneously in some controlled studies and using a checklist in other studies. The overall profile of adverse events was similar using either method. shows those events that occurred in any Campral treatment group at a rate of 3% or greater and greater than the placebo group in controlled clinical trials with spontaneously reported adverse events. The reported frequencies of adverse events represent the proportion of individuals who experienced, at least once, a treatment-emergent adverse event of the type listed, without regard to the causal relationship of the events to the drug. Table 1

Table 1. Events Occurring at a Rate of at Least 3% and Greater than Placebo in any Campral Treatment Group in Controlled Clinical Trials with Spontaneously Reported Adverse Events.
Body System/Preferred Term | Number of Patients (%) with Events
Body System/Preferred Term | Campral 1332 mg/day | Campral 1998 mg/day ^1 | Campral Pooled ^2 | Placebo
Number of patients in Treatment Group | 397 | 1539 | 2019 | 1706
Number (%) of patients with an AE | 248 (62%) | 910 (59%) | 1231 (61%) | 955 (56%)
Body as a Whole | 121 (30%) | 513 (33%) | 685 (34%) | 517 (30%)
Accidental Injury*† | 17 (4%) | 44 (3%) | 70 (3%) | 52 (3%)
Asthenia | 29 (7%) | 79 (5%) | 114 (6%) | 93 (5%)
Pain | 6 (2%) | 56 (4%) | 65 (3%) | 55 (3%)
Digestive System | 85 (21%) | 440 (29%) | 574 (28%) | 344 (20%)
Anorexia | 20 (5%) | 35 (2%) | 57 (3%) | 44 (3%)
Diarrhea | 39 (10%) | 257 (17%) | 329 (16%) | 166 (10%)
Flatulence | 4 (1%) | 55 (4%) | 63 (3%) | 28 (2%)
Nausea | 11 (3%) | 69 (4%) | 87 (4%) | 58 (3%)
Nervous System | 150 (38%) | 417 (27%) | 598 (30%) | 500 (29%)
Anxiety††** | 32 (8%) | 80 (5%) | 118 (6%) | 98 (6%)
Depression | 33 (8%) | 63 (4%) | 102 (5%) | 87 (5%)
Dizziness | 15 (4%) | 49 (3%) | 67 (3%) | 44 (3%)
Dry mouth | 13 (3%) | 23 (1%) | 36 (2%) | 28 (2%)
Insomnia | 34 (9%) | 94 (6%) | 137 (7%) | 121 (7%)
Paresthesia | 11 (3%) | 29 (2%) | 40 (2%) | 34 (2%)
Skin and Appendages | 26 (7%) | 150 (10%) | 187 (9%) | 169 (10%)
Pruritus | 12 (3%) | 68 (4%) | 82 (4%) | 58 (3%)
Sweating | 11 (3%) | 27 (2%) | 40 (2%) | 39 (2%)
†*includes events coded as “fracture” by sponsor; ††**includes events coded as “nervousness” by sponsor
includes 258 patients treated with acamprosate calcium 2000 mg/day, using a different dosage strength and regimen.^1
includes all patients in the first two columns as well as 83 patients treated with acamprosate calcium 3000 mg/day, using a different dosage strength and regimen.^2

Concomitant Therapies

In clinical trials, the safety profile in subjects treated with Campral concomitantly with anxiolytics, hypnotics and sedatives (including benzodiazepines), or non-opioid analgesics was similar to that of subjects taking placebo with these concomitant medications. Patients taking Campral concomitantly with antidepressants more commonly reported both weight gain and weight loss, compared with patients taking either medication alone.

Other Events Observed During the Premarketing Evaluation of Campral

Following is a list of terms that reflect treatment-emergent adverse events reported by patients treated with Campral in 20 clinical trials (4461 patients treated with Campral, 3526 of whom received the maximum recommended dose of 1998 mg/day for up to one year in duration). This listing does not include those events already listed above; events for which a drug cause was considered remote; event terms which were so general as to be uninformative; and events reported only once which were not likely to be acutely life-threatening.

Events are further categorized by body system and listed in order of decreasing frequency according to the following definitions: frequent adverse events are those occurring in at least 1/100 patients (only those not already listed in the summary of adverse events in controlled trials appear in this listing); infrequent adverse events are those occurring in 1/100 to 1/1000 patients; rare events are those occurring in fewer than 1/1000 patients.

: headache, abdominal pain, back pain, infection, flu syndrome, chest pain, chills, suicide attempt; : fever, intentional overdose, malaise, allergic reaction, abscess, neck pain, hernia, intentional injury; : ascites, face edema, photosensitivity reaction, abdomen enlarged, sudden death. Body as a Whole –Frequent Infrequent Rare

: palpitation, syncope; : hypotension, tachycardia, hemorrhage, angina pectoris, migraine, varicose vein, myocardial infarct, phlebitis, postural hypotension; : heart failure, mesenteric arterial occlusion, cardiomyopathy, deep thrombophlebitis, shock. Cardiovascular System –Frequent Infrequent Rare

: vomiting, dyspepsia, constipation, increased appetite; : liver function tests abnormal, gastroenteritis, gastritis, dysphagia, eructation, gastrointestinal hemorrhage, pancreatitis, rectal hemorrhage, liver cirrhosis, esophagitis, hematemesis, nausea and vomiting, hepatitis; melena, stomach ulcer, cholecystitis, colitis, duodenal ulcer, mouth ulceration, carcinoma of liver. Digestive System –Frequent Infrequent Rare:

goiter, hypothyroidism. Endocrine System –Rare:

: anemia, ecchymosis, eosinophilia, lymphocytosis, thrombocytopenia; leukopenia, lymphadenopathy, monocytosis. Hemic and Lymphatic System –Infrequent Rare:

– peripheral edema, weight gain; : weight loss, hyperglycemia, SGOT increased, SGPT increased, gout, thirst, hyperuricemia, diabetes mellitus, avitaminosis, bilirubinemia; alkaline phosphatase increased, creatinine increased, hyponatremia, lactic dehydrogenase increased. Metabolic and Nutritional Disorders –Frequent Infrequent Rare:

– myalgia, arthralgia; : leg cramps; rheumatoid arthritis, myopathy. Musculoskeletal System –Frequent Infrequent Rare:

–somnolence, libido decreased, amnesia, thinking abnormal, tremor, vasodilatation, hypertension; : convulsion, confusion, libido increased, vertigo, withdrawal syndrome, apathy, suicidal ideation, neuralgia, hostility, agitation, neurosis, abnormal dreams, hallucinations, hypesthesia; : alcohol craving, psychosis, hyperkinesia, twitching, depersonalization, increased salivation, paranoid reaction, torticollis, encephalopathy, manic reaction. Nervous System –Frequent Infrequent Rare

: rhinitis, cough increased, dyspnea, pharyngitis, bronchitis; : asthma, epistaxis, pneumonia; laryngismus, pulmonary embolus. Respiratory System –Frequent Infrequent Rare:

: rash; : acne, eczema, alopecia, maculopapular rash, dry skin, urticaria, exfoliative dermatitis, vesiculobullous rash; psoriasis. Skin and Appendages –Frequent Infrequent Rare:

: abnormal vision, taste perversion; : tinnitus, amblyopia, deafness; ophthalmitis, diplopia, photophobia. Special Senses –Frequent Infrequent Rare:

: impotence; – metrorrhagia, urinary frequency, urinary tract infection, sexual function abnormal, urinary incontinence, vaginitis; kidney calculus, abnormal ejaculation, hematuria, menorrhagia, nocturia, polyuria, urinary urgency. Urogenital System –Frequent Infrequent Rare:

6.2 Postmarketing Experience

The following adverse reactions have been identified during post approval use of Campral. Because these reactions are reported voluntarily from a population of uncertain size, it is not always possible to reliably estimate their frequency or establish a causal relationship to drug exposure.

Serious Adverse Events Observed During the Non-US Postmarketing Evaluation of Campral (acamprosate calcium)

The serious adverse event of acute kidney failure has been reported to be temporally associated with Campral treatment in at least 3 patients and is not described elsewhere in the labeling.

7 DRUG INTERACTIONS

Acamprosate does not affect the pharmacokinetics of alcohol. The pharmacokinetics of acamprosate are not affected by alcohol, diazepam, or disulfiram, and clinically important interactions between naltrexone and acamprosate were not observed [ ]. see Clinical Pharmacology () 12.3

8 USE IN SPECIFIC POPULATIONS

8.1 Pregnancy

Pregnancy Category C

TERATOGENIC EFFECTS

Acamprosate calcium has been shown to be teratogenic in rats when given in doses that are approximately equal to the human dose (on a mg/m basis) and in rabbits when given in doses that are approximately 3 times the human dose (on a mg/m basis). Acamprosate calcium produced a dose-related increase in the number of fetuses with malformations in rats at oral doses of 300 mg/kg/day or greater (approximately equal to the maximum recommended human daily (MRHD) oral dose on a mg/m basis). The malformations included hydronephrosis, malformed iris, retinal dysplasia, and retroesophageal subclavian artery. No findings were observed at an oral dose of 50 mg/kg/day (approximately one-fifth the MRHD oral dose on a mg/m basis). An increased incidence of hydronephrosis was also noted in Burgundy Tawny rabbits at oral doses of 400 mg/kg/day or greater (approximately 3 times the MRHD oral dose on a mg/m basis). No developmental effects were observed in New Zealand white rabbits at oral doses up to 1000 mg/kg/day (approximately 8 times the MRHD oral dose on a mg/m basis). The findings in animals should be considered in relation to known adverse developmental effects of ethyl alcohol, which include the characteristics of fetal alcohol syndrome (craniofacial dysmorphism, intrauterine and postnatal growth retardation, retarded psychomotor and intellectual development) and milder forms of neurological and behavioral disorders in humans. There are no adequate and well controlled studies in pregnant women. Campral should be used during pregnancy only if the potential benefit justifies the potential risk to the fetus. Teratogenic effects:^2^2^2^2^2^2

NONTERATOGENIC EFFECTS

A study conducted in pregnant mice that were administered acamprosate calcium by the oral route starting on Day 15 of gestation through the end of lactation on postnatal day 28 demonstrated an increased incidence of still-born fetuses at doses of 960 mg/kg/day or greater (approximately 2 times the MRHD oral dose on a mg/m basis). No effects were observed at a dose of 320 mg/kg/day (approximately one-half the MRHD dose on a mg/m basis). Nonteratogenic effects:^2^2

8.2 Labor and Delivery

The potential for Campral to affect the duration of labor and delivery is unknown.

8.3 Nursing Mothers

In animal studies, acamprosate was excreted in the milk of lactating rats dosed orally with acamprosate calcium. The concentration of acamprosate in milk compared to blood was 1.3:1. It is not known whether acamprosate is excreted in human milk. Because many drugs are excreted in human milk, caution should be exercised when Campral is administered to a nursing woman.

8.4 Pediatric Use

The safety and efficacy of Campral have not been established in the pediatric population.

8.5 Geriatric Use

Forty-one of the 4234 patients in double-blind, placebo-controlled, clinical trials of Campral were 65 years of age or older, while none were 75 years of age or over. There were too few patients in the ≥65 age group to evaluate any differences in safety or effectiveness for geriatric patients compared to younger patients.

This drug is known to be substantially excreted by the kidney, and the risk of toxic reactions to this drug may be greater in patients with impaired renal function. Because elderly patients are more likely to have decreased renal function, care should be taken in dose selection, and it may be useful to monitor renal function and ]. [see Clinical Pharmacology (), Adverse Reactions (), 12.36.1 Dosage and Administration () 2.1

8.6 Renal Impairment

Campral is contraindicated in patients with severe renal impairment (creatinine clearance of ≤30 mL/min) [s and ]. ee Dosage and Administration (), Contraindications (), Warnings and Precautions (), 2.14.25.1 Clinical Pharmacology () 12.3

10 OVERDOSAGE

In all reported cases of acute overdosage with Campral (total reported doses of up to 56 grams of acamprosate calcium), the only symptom that could be reasonably associated with Campral was diarrhea. Hypercalcemia has not been reported in cases of acute overdose. A risk of hypercalcemia should be considered in chronic overdosage only. Treatment of overdose should be symptomatic and supportive.

11 DESCRIPTION

Campral (acamprosate calcium) is supplied in an enteric-coated tablet for oral administration. Acamprosate calcium is a synthetic compound with a chemical structure similar to that of the endogenous amino acid homotaurine, which is a structural analogue of the amino acid neurotransmitter γ-aminobutyric acid and the amino acid neuromodulator taurine. Its chemical name is calcium acetylaminopropane sulfonate. Its chemical formula is C H N O S Ca and molecular weight is 400.48. Its structural formula is:1020282

Acamprosate calcium is a white, odorless or nearly odorless powder. It is freely soluble in water, and practically insoluble in absolute ethanol and dichloromethane.

Each Campral tablet contains acamprosate calcium 333 mg, equivalent to 300 mg of acamprosate. Inactive ingredients in Campral tablets include: crospovidone, microcrystalline cellulose, magnesium silicate, sodium starch glycolate, colloidal anhydrous silica, magnesium stearate, talc, propylene glycol and Eudragit L 30 D or equivalent. Sulfites were used in the synthesis of the drug substance and traces of residual sulfites may be present in the drug product.®

12 CLINICAL PHARMACOLOGY

12.1 Mechanism of Action

The mechanism of action of acamprosate in maintenance of alcohol abstinence is not completely understood. Chronic alcohol exposure is hypothesized to alter the normal balance between neuronal excitation and inhibition. and studies in animals have provided evidence to suggest acamprosate may interact with glutamate and GABA neurotransmitter systems centrally, and has led to the hypothesis that acamprosate restores this balance. In vitroin vivo

12.2 Pharmacodynamics

Pharmacodynamic studies have shown that acamprosate calcium reduces alcohol intake in alcohol-dependent animals in a dose-dependent manner and that this effect appears to be specific to alcohol and the mechanisms of alcohol dependence.

Acamprosate calcium has negligible observable central nervous system (CNS) activity in animals outside of its effects on alcohol dependence, exhibiting no anticonvulsant, antidepressant, or anxiolytic activity.

The administration of acamprosate calcium is not associated with the development of tolerance or dependence in animal studies. Campral did not produce any evidence of withdrawal symptoms in patients in clinical trials at therapeutic doses. Post marketing data, collected retrospectively outside the U.S. have provided no evidence of Campral abuse or dependence.

Campral is not known to cause alcohol aversion and does not cause a disulfiram-like reaction as a result of ethanol ingestion.

12.3 Pharmacokinetics

Absorption

The absolute bioavailability of Campral after oral administration is about 11%. Steady-state plasma concentrations of acamprosate are reached within 5 days of dosing. Steady-state peak plasma concentrations after Campral doses of 2 x 333 mg tablets three times daily average 350 ng/mL and occur at 3-8 hours post-dose. Coadministration of Campral with food decreases bioavailability as measured by C and AUC, by approximately 42% and 23%, respectively. The food effect on absorption is not clinically significant and no adjustment of dose is necessary.max

Distribution

The volume of distribution for acamprosate following intravenous administration is estimated to be 72-109 liters (approximately 1 L/kg). Plasma protein binding of acamprosate is negligible.

Metabolism

Acamprosate does not undergo metabolism.

Elimination

After oral dosing of 2 x 333 mg of Campral, the terminal half-life ranges from approximately 20-33 hours. Following oral administration of Campral, the major route of excretion is via the kidneys as acamprosate.

Special Populations

Campral does not exhibit any significant pharmacokinetic differences between male and female subjects. Gender:

The pharmacokinetics of Campral have not been evaluated in a geriatric population. However, since renal function diminishes in elderly patients and acamprosate is excreted unchanged in urine, acamprosate plasma concentrations are likely to be higher in the elderly population compared to younger adults. Age:

The pharmacokinetics of Campral have not been evaluated in a pediatric population. Pediatrics:

: Peak plasma concentrations after administration of a single dose of 2 x 333 mg Campral tablets to patients with moderate or severe renal impairment were about 2-fold and 4-fold higher, respectively, compared to healthy subjects. Similarly, elimination half-life was about 1.8-fold and 2.6-fold longer, respectively, compared to healthy subjects. There is a linear relationship between creatinine clearance values and total apparent plasma clearance, renal clearance and plasma half-life of acamprosate. A dose of 1 x 333 mg Campral, three times daily, is recommended in patients with moderate renal impairment (creatinine clearance of 30-50 mL/min, [ ]. Renal Impairmentsee Use in Specific Populations () 8.6

Campral is contraindicated in patients with severe renal impairment (creatinine clearance of ≤30 mL/min) [ and ]. see Dosage and Administration (), Contraindications (), Warnings and Precautions (), 2.14.25.1 Use in Specific Populations () 8.6

: Acamprosate is not metabolized by the liver and the pharmacokinetics of Campral are not altered in patients with mild to moderate hepatic impairment (groups A and B of the Child-Pugh classification). No adjustment of dosage is recommended in such patients. Hepatic Impairment

: A cross-study comparison of Campral at doses of 2 x 333 mg three times daily indicated similar pharmacokinetics between alcohol-dependent subjects and healthy subjects. Alcohol-dependent subjects

Drug-Drug Interactions

Acamprosate had no inducing potential on the cytochrome CYP1A2 and 3A4 systems, and inhibition studies suggest that acamprosate does not inhibit metabolism mediated by cytochrome CYP1A2, 2C9, 2C19, 2D6, 2E1, or 3A4. The pharmacokinetics of Campral were unaffected when co-administered with alcohol, disulfiram or diazepam. Similarly, the pharmacokinetics of ethanol, diazepam and nordiazepam, imipramine and desipramine, naltrexone and 6-beta naltrexol were unaffected following co-administration with Campral. However, co-administration of Campral with naltrexone led to a 33% increase in the C and a 25% increase in the AUC of acamprosate. No adjustment of dosage is recommended in such patients. in vitroin vivomax

13 NONCLINICAL TOXICOLOGY

13.1 Carcinogenesis, Mutagenesis, Impairment of Fertility

Dietary administration of acamprosate calcium for 2 years to Sprague-Dawley rats at doses of 25, 100 and 400 mg/kg/day (up to 3 times the maximum recommended human daily (MRHD) oral dose on an AUC basis) and CD-1 mice at doses of 400, 1200 and 3600 mg/kg/day (up to 25 times the MRHD on an AUC basis) showed no evidence of increased tumor incidence.

Acamprosate calcium was negative in all genetic toxicology studies conducted. Acamprosate calcium demonstrated no evidence of genotoxicity in an bacterial reverse point mutation assay (Ames assay) or an mammalian cell gene mutation test using Chinese Hamster Lung V79 cells. No clastogenicity was observed in an chromosomal aberration assay in human lymphocytes and no chromosomal damage detected in an mouse micronucleus assay. in vitroin vitroin vitroin vivo

Acamprosate calcium had no effect on fertility after treatment for 70 days prior to mating in male rats and for 14 days prior to mating, throughout mating, gestation and lactation in female rats at doses up to 1000 mg/kg/day (approximately 4 times the MRHD oral dose on a mg/m basis). In mice, acamprosate calcium administered orally for 60 days prior to mating and throughout gestation in females at doses up to 2400 mg/kg/day (approximately 5 times the MRHD oral dose on a mg/m basis) had no effect on fertility.^2^2

14 CLINICAL STUDIES

The efficacy of Campral in the maintenance of abstinence was supported by three clinical studies involving a total of 998 patients who were administered at least one dose of Campral or placebo as an adjunct to psychosocial therapy. Each study was a double-blind, placebo-controlled trial in alcohol-dependent patients who had undergone inpatient detoxification and were abstinent from alcohol on the day of randomization. Study durations ranged from 90 days to 360 days. Campral proved superior to placebo in maintaining abstinence, as indicated by a greater percentage of subjects being assessed as continuously abstinent throughout treatment.

In a fourth study, the efficacy of Campral was evaluated in alcoholics, including patients with a history of polysubstance abuse and patients who had not undergone detoxification and were not required to be abstinent at baseline. This study failed to demonstrate superiority of Campral over placebo.

16 HOW SUPPLIED/STORAGE AND HANDLING

NDC:68151-4760-0 in a PACKAGE of 1 TABLET, DELAYED RELEASES

Storage and Handling

Store at 25ºC (77ºF); excursions permitted to 15º to 30ºC (59º to 86ºF).

17 PATIENT COUNSELING INFORMATION

17.1 Information for Patients

Physicians are advised to discuss the following issues with patients for whom they prescribe Campral.

Renal Impairment

A lower dose is recommended for patients with moderate renal impairment. Campral is contraindicated in patients with severe renal impairment (creatine clearance of ≤30 mL/min) [ ]. see Dosage and Administration (), Contraindications (), Warnings and Precautions () and Use in Specific Populations () 2.14.25.18.6

Suicidality and Depression

Families and caregivers of patients being treated with Campral should be alerted to the need to monitor patients for the emergence of symptoms of depression or suicidality, and to report such symptoms to the patient's health care provider [ ]. see Warnings and Precautions () 5.2

Alcohol Withdrawal

Use of Campral does not eliminate or diminish withdrawal symptoms [ ]. see Warnings and Precautions () 5.3

Pregnancy and Breast Feeding

- Advise patients to notify their physician if they become pregnant or intend to become pregnant during therapy.
- Advise patients to notify their physician if they are breast-feeding.

Relapse to Drinking

- Advise patients to continue Campral therapy as directed, even in the event of relapse and remind them to discuss any renewed drinking with their physicians.
- Advise patients that Campral has been shown to help maintain abstinence only when used as a part of a treatment program that includes counseling and support.

Manufactured by: Merck Santé s.a.s. Subsidiary of Merck KGaA, Darmstadt, Germany 37, rue Saint-Romain 69008 LYON FRANCE

Manufactured for: Forest Pharmaceuticals, Inc. Subsidiary of Forest Laboratories, Inc. St. Louis, MO 63045